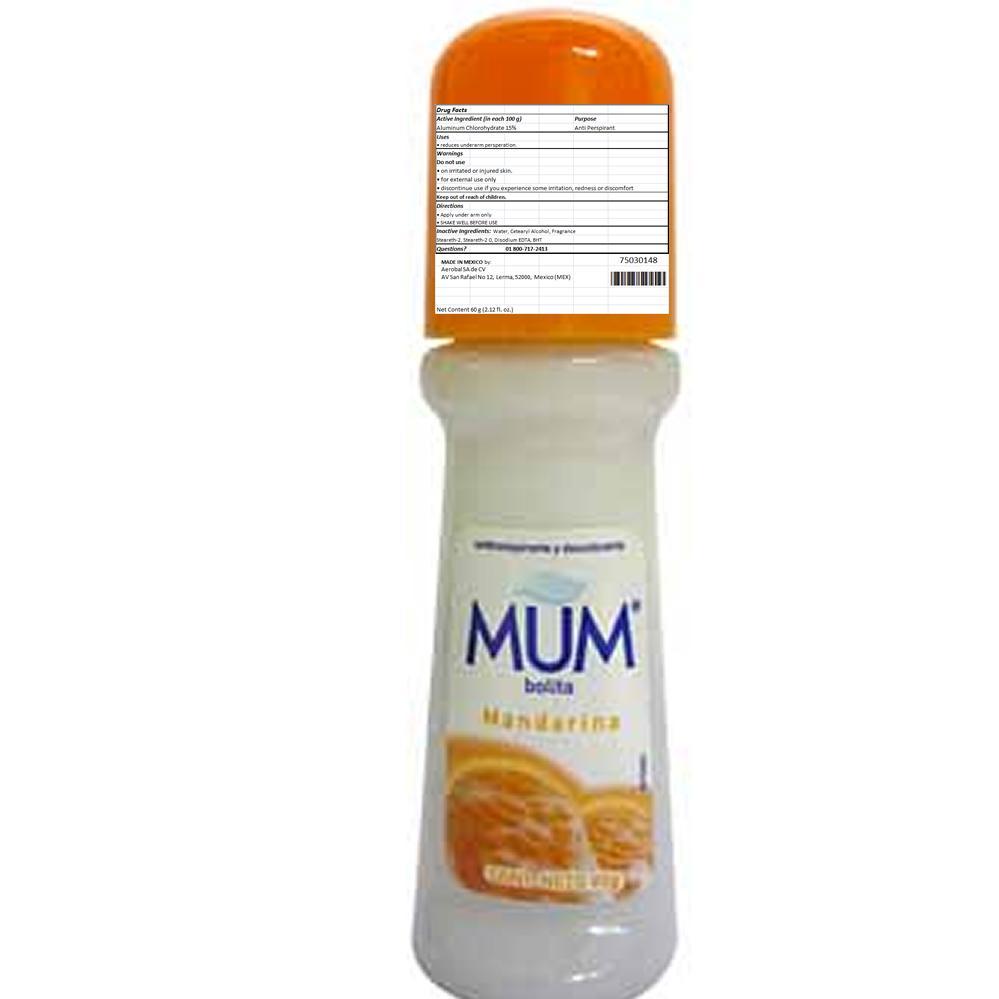 DRUG LABEL: MUM CHAMOMILE
NDC: 51769-555 | Form: STICK
Manufacturer: ALL NATURAL DYNAMICS
Category: otc | Type: HUMAN OTC DRUG LABEL
Date: 20130829

ACTIVE INGREDIENTS: Aluminum Chlorohydrate 15 g/100 g
INACTIVE INGREDIENTS: Water; CETOSTEARYL ALCOHOL; EDETATE DISODIUM

MUM CHAMOMILE

Warnings:

For External Use Only. Do Not Apply On Irritated Or Injured Skin. Discontinue Use If You Experience Some Irritation, Redness Or Discomfort.

Active Ingredient:

Aluminum Chlorohydrate 15%

Purpose

Anti Perspirant

Keep Out Of The Reach Of Children

USE:

reduces underarm persperation

Directions:

Apply under arm only.

SHAKE WELL BEFORE USE.

Inactive Ingredients:

Water, soy oil, steareth-2 PPG-15 stearyl ether, steareth-20, fragrance, caprillglycol, Xanlein, (Xyitol, lemon extract-citrus medicalimonum), fruit extract carica papaya (papaya) olea leaf extract (olive) tetrasodium EDTA and BHT